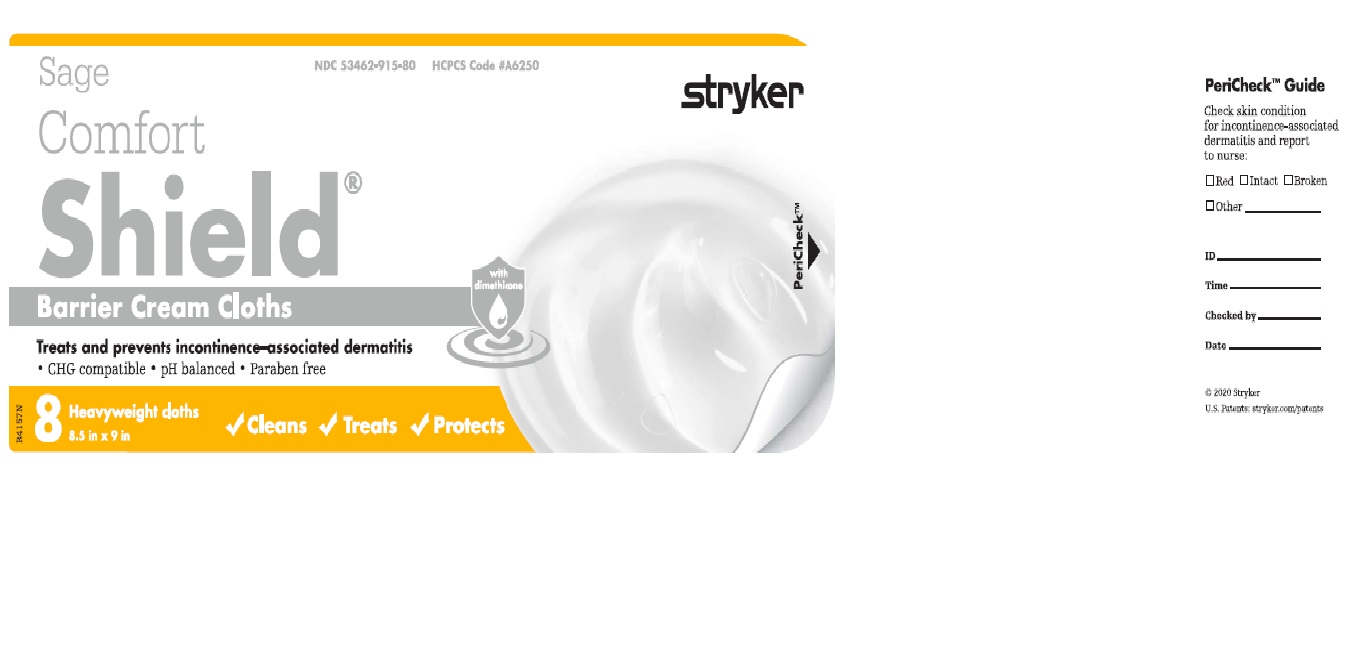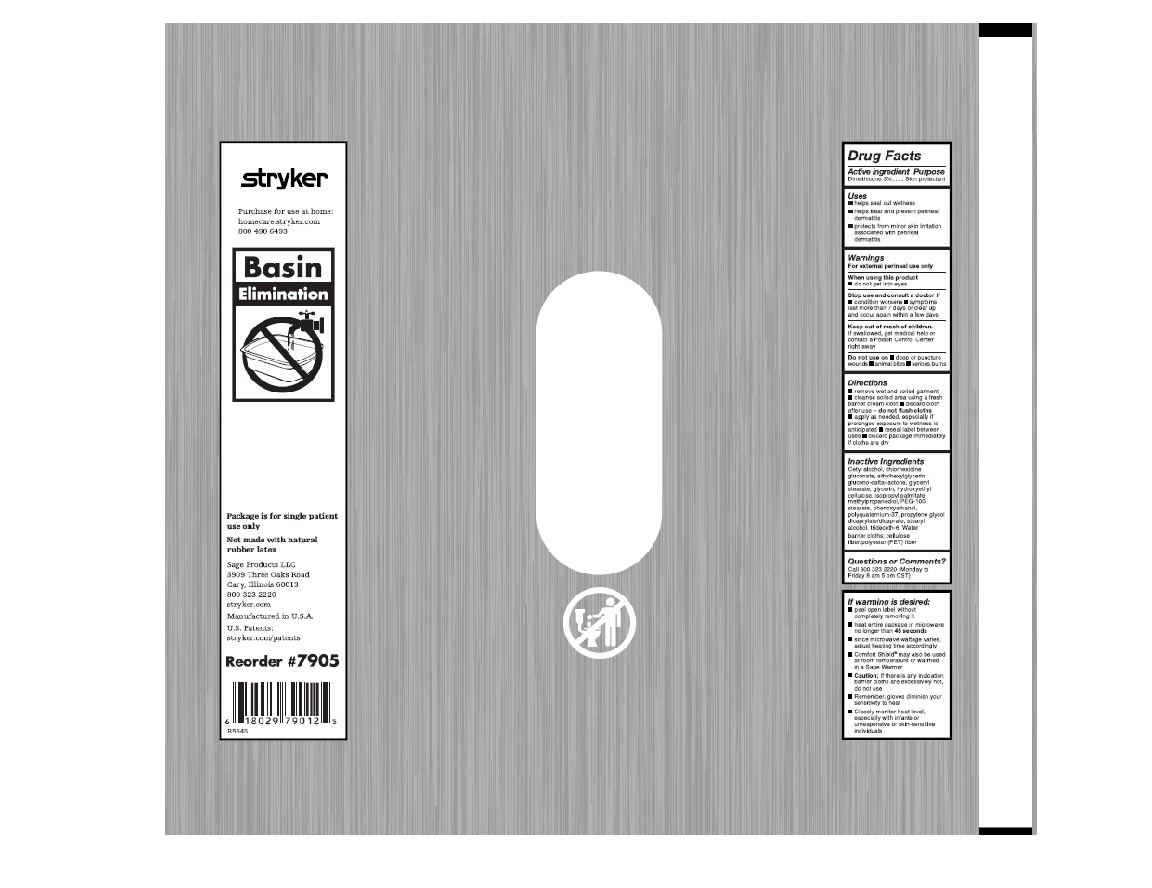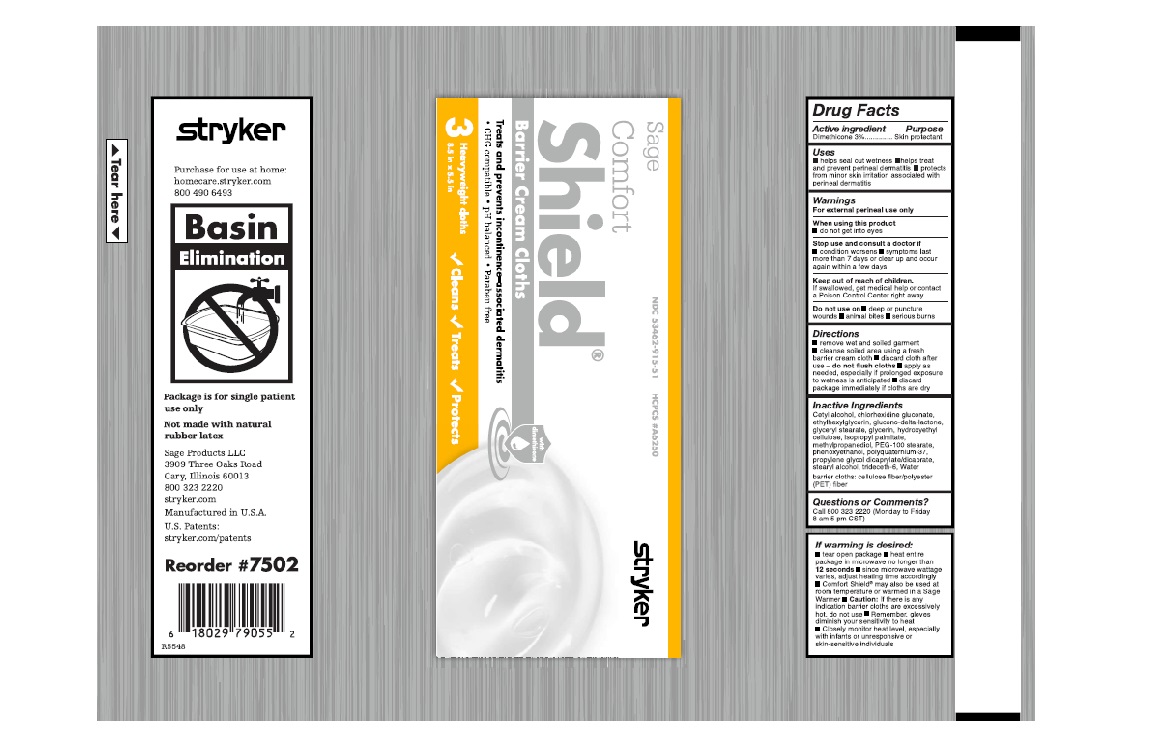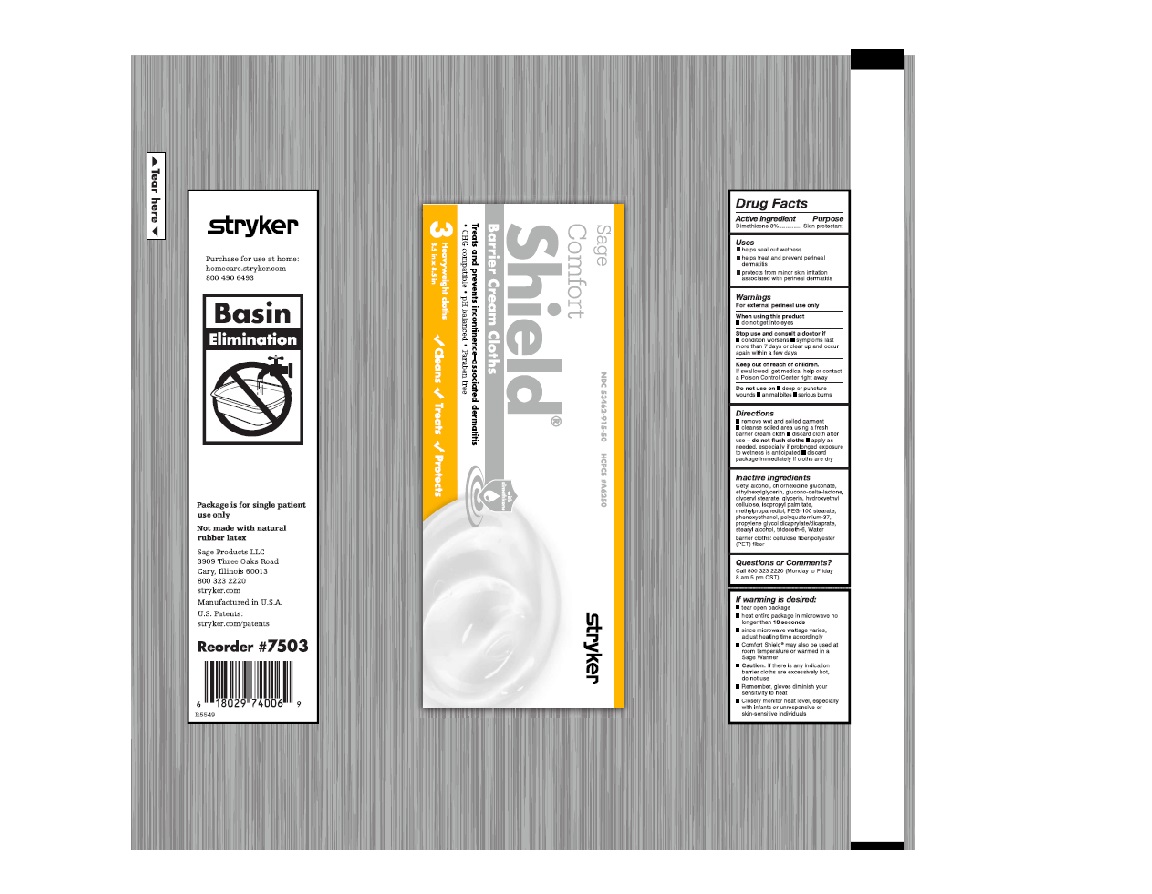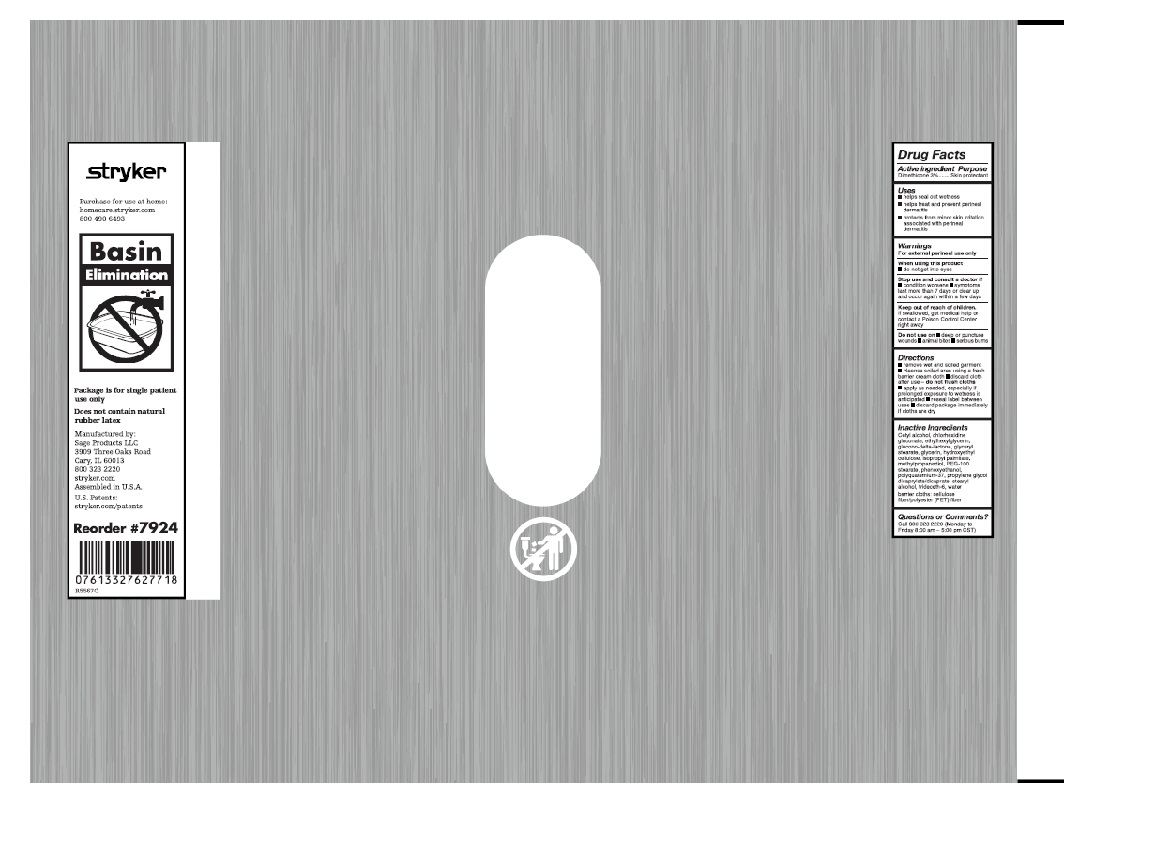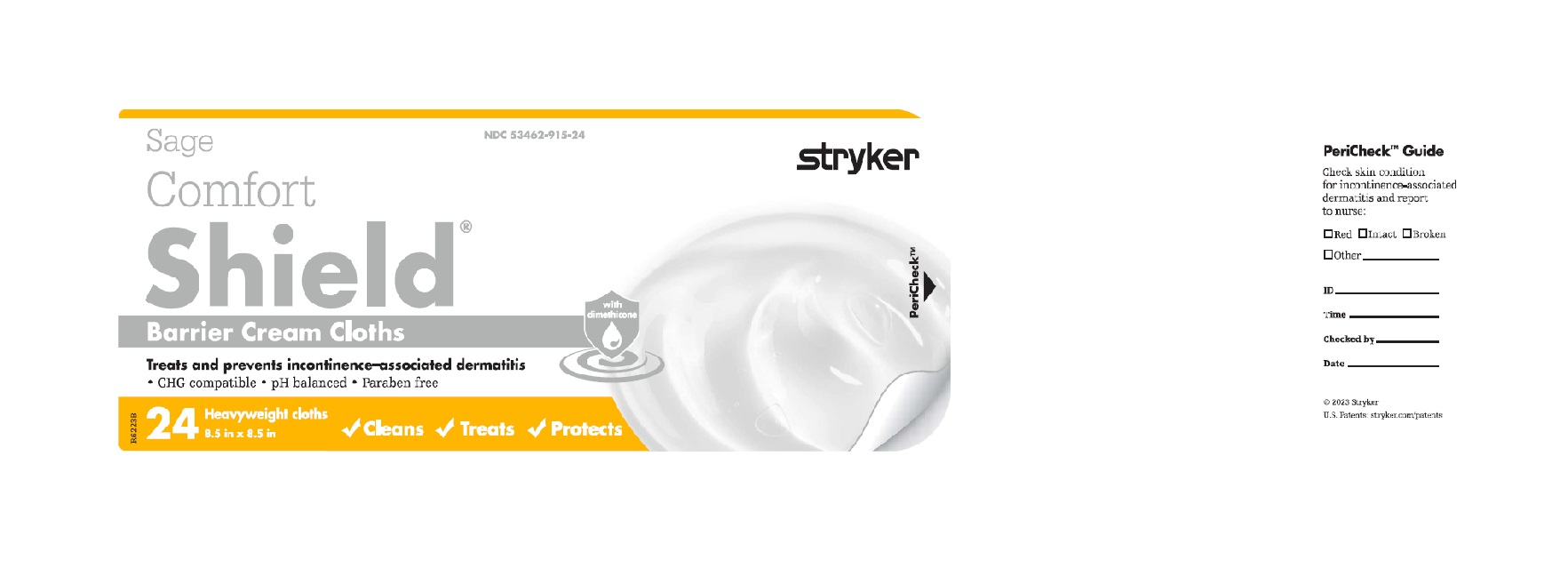 DRUG LABEL: Comfort Shield Barrier
NDC: 53462-915 | Form: CLOTH
Manufacturer: Sage Products LLC
Category: otc | Type: HUMAN OTC DRUG LABEL
Date: 20251020

ACTIVE INGREDIENTS: DIMETHICONE 30 mg/1 g
INACTIVE INGREDIENTS: WATER; GLYCERYL MONOSTEARATE; PEG-100 STEARATE; ISOPROPYL PALMITATE; CETYL ALCOHOL; GLYCERIN; STEARYL ALCOHOL; PHENOXYETHANOL; METHYLPROPANEDIOL; CHLORHEXIDINE GLUCONATE; HYDROXYETHYL CELLULOSE (4000 MPA.S AT 1%); ETHYLHEXYLGLYCERIN; POLYQUATERNIUM-37 (25000 MPA.S); PROPYLENE GLYCOL DICAPRYLATE/DICAPRATE; GLUCONOLACTONE; PPG-1 TRIDECETH-6

Comfort Shield Barrier Cream Cloths

Active Ingredient

Dimethicone 3%

Purpose

Skin protectant

Uses

- helps seal out wetness
- helps treat and prevent perineal dermatitis
- protects from minor skin irritation associated with perineal dermatitis

Warnings

For external perineal use only.
Avoid contact with the eyes.

Stop use and consult a doctor if condition worsens or does not improve within 7 days

Keep out of reach of children.

If swallowed, get medical help or contact a Poison Control Center right away

Directions

- remove wet and soiled garment
- cleanse soiled area using a fresh barrier cream cloth
- discard cloth after use - DO NOT FLUSH CLOTHS
- use as often as necessary, especially if prolonged exposure to wetness is anticipated
- for individual use only
- reseal label between uses
- discard package immediately if cloths are dry

If warming is desired:

- peel open label without completely removing it
- heat entire package in microwave no longer than [see package for time].
- since microwave wattage varies, adjust heating time accordingly
- Comfort Shield® may also be used at room temperature or warmed in a Comfort Personal Cleansing Warmer.
- Caution: If there is any indication barrier cloths are excessively hot, do not use
- Remember, gloves diminish your sensitivity to heat
- Closely monitor heat level with infants, unresponsive or skin sensitive individuals

Inactive Ingredients

Water, glyceryl stearate, PEG-100 stearate, isopropyl palmitate, cetyl alcohol, glycerin, stearyl alcohol, phenoxyethanol, methylpropanediol, chlorhexidine gluconate, hydroxyethyl cellulose, ethylhexylglycerin, polyquaternium-37, propylene glycol dicaprylate/dicaprate, glucono-delta-lactone, PPG-1 trideceth-6

Barrier cloths: cellulose fiber/polyester (PET) fiber

Questions or Comments?

800-323-2220